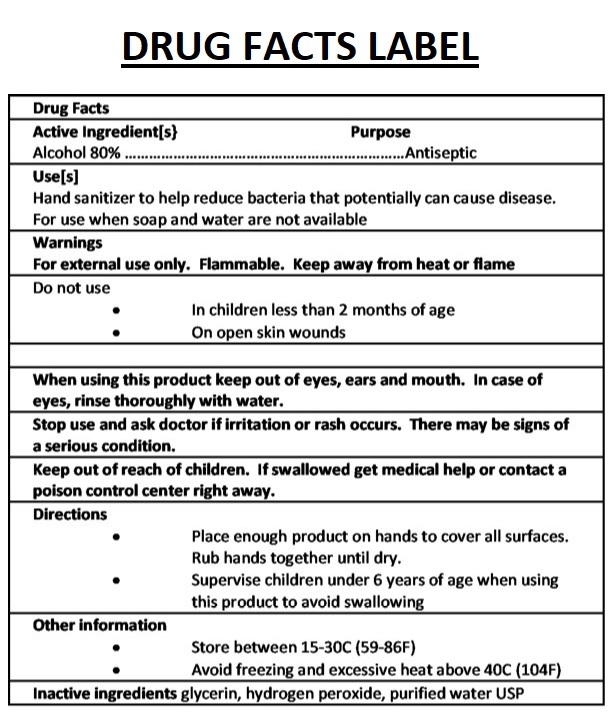 DRUG LABEL: MCL Hand Sanitizer
NDC: 80411-001 | Form: LIQUID
Manufacturer: Midcontinental Compounding Laboratory LLC
Category: otc | Type: HUMAN OTC DRUG LABEL
Date: 20200907

ACTIVE INGREDIENTS: ALCOHOL 80 mL/100 mL
INACTIVE INGREDIENTS: GLYCERIN; HYDROGEN PEROXIDE; WATER

MCL Hand Sanitizer

Active Ingredients[s}

Alcohol 80%

Purpose

Antiseptic

Use[s]

Hand sanitizer to help reduce bacteria that potentially can cause disease.

For use when soap and water are not available

Warnings

For external use only. Flammable. Keep away from heat or flame.

Do not use

• In children less than 2 months of age

• On open skin wounds

When using this product keep out of eyes, ears and mouth. In case of eyes, rinse thoroughly with water.

Stop useand ask doctor if irritation or rash occurs. There may be signs of a serious condition.

Keep out of reach of children. If swallowed get medical help or contact a poison control center right away.

Directions

• Place enough product on hands to cover all surfaces.

Rub hands together until dry.

• Supervise children under 6 years of age when using this product to avoid swallowing

Other information

• Store between 15-30C (59-86F)

• Avoid freezing and excessive heat above 40C (104F)

Inactive ingredients glycerin, hydrogen peroxide, purified water USP